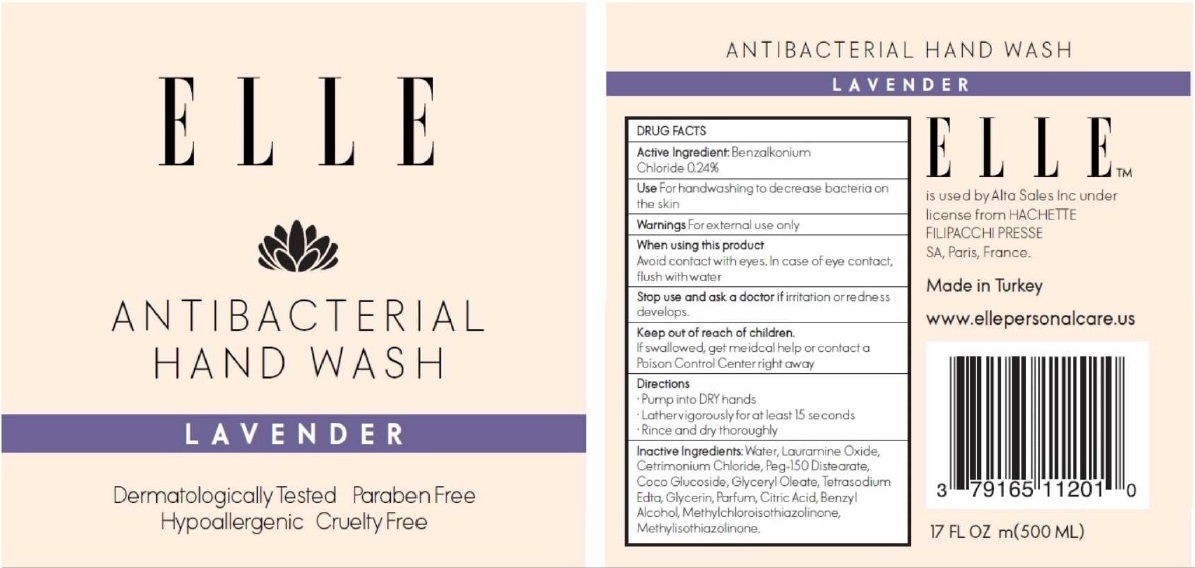 DRUG LABEL: ELLE ANTIBACTERIAL HAND WASH
NDC: 79165-112 | Form: LIQUID
Manufacturer: Alta Sales Inc
Category: otc | Type: HUMAN OTC DRUG LABEL
Date: 20200903

ACTIVE INGREDIENTS: BENZALKONIUM CHLORIDE 0.24 g/100 mL
INACTIVE INGREDIENTS: WATER; LAURAMINE OXIDE; CETRIMONIUM CHLORIDE; PEG-150 DISTEARATE; COCO GLUCOSIDE; GLYCERYL OLEATE; EDETATE SODIUM; GLYCERIN; CITRIC ACID MONOHYDRATE; BENZYL ALCOHOL; METHYLCHLOROISOTHIAZOLINONE; METHYLISOTHIAZOLINONE

ELLE ANTIBACTERIAL HAND WASH LAVENDER

Active Ingredient: Benzalkonium Chloride 0.24%

Purpose: Antiseptic

INDICATIONS AND USAGE

Use For handwashing to decrease bacteria on the skin

Warnings For external use only

When using this product
Avoid contact with eyes. In case of eye contact, flush with water

Stop use and ask a doctor if irritation or redness develops.

Keep out of reach of children.
If swallowed, get medical help or contact a Poison Control Center right away

Directions

• Pump into DRY hands
• Lather vigorously for at least 15 seconds
• Rinse and dry thoroughly

INACTIVE INGREDIENT

Inactive Ingredients: Water, Lauramine Oxide, Cetrimonium Chloride, Peg-150 Distearate, Coco Glucoside, Glyceryl Oleate, Tetrasodium Edta, Glycerin, Parfum, Citric Acid, Benzyl Alcohol, Methylchloroisothiazolinone, Methylisothiazolinone.

Dermatologically Tested

Paraben Free

Hypoallergenic

Cruelty Free

ELLE™ is used by Alta Sales Inc under license from HACHETTE FILIPACCHI PRESSE SA, Paris, France.
Made in Turkey
www.ellepersonalcare.us